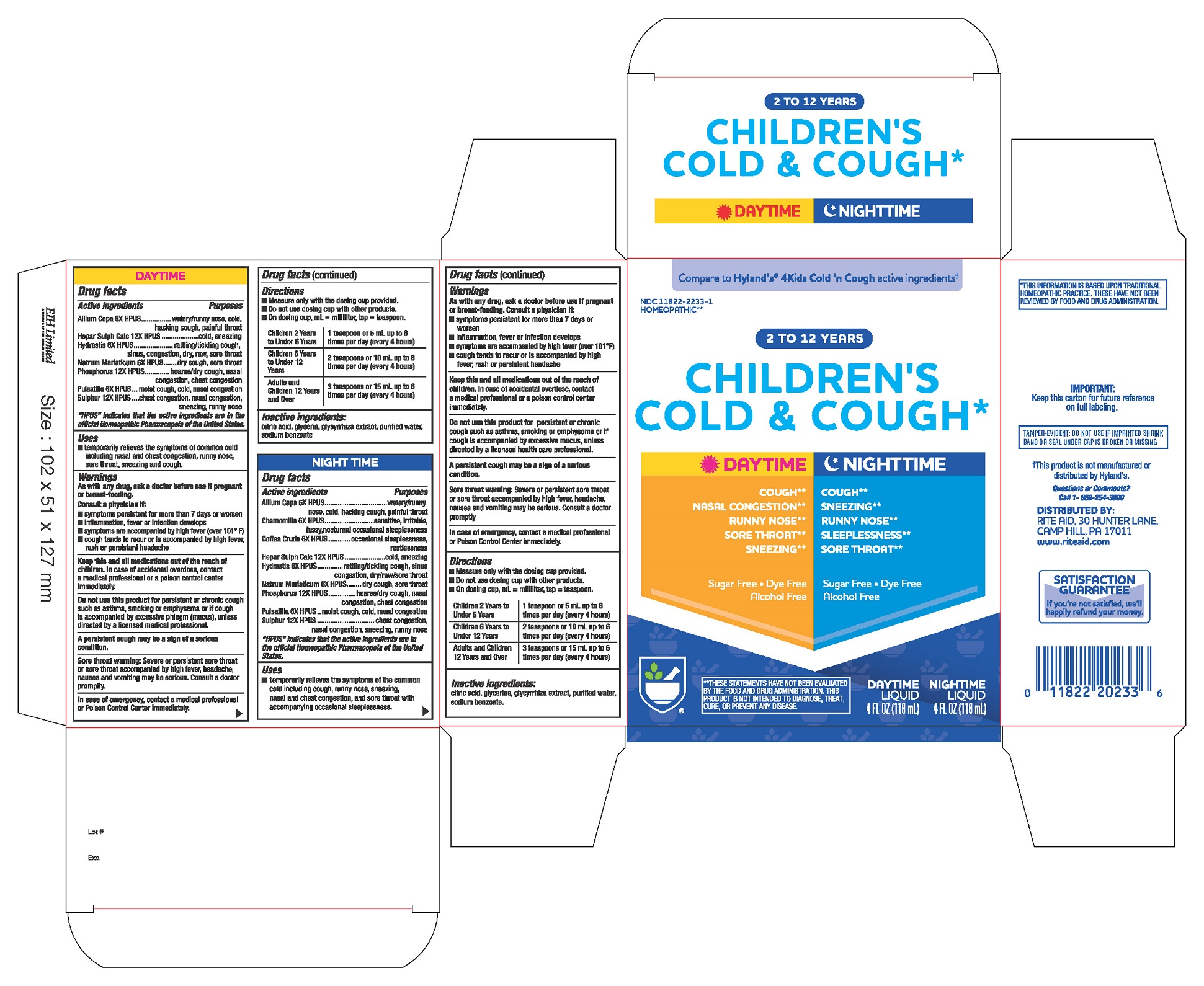 DRUG LABEL: 2 to 12 YEARS CHILDRENS COLD and COUGH DAY and NIGHT TIME
NDC: 11822-2233 | Form: KIT | Route: ORAL
Manufacturer: Rite Aid Hdgrts Corp
Category: homeopathic | Type: HUMAN OTC DRUG LABEL
Date: 20241227

ACTIVE INGREDIENTS: ONION 6 [hp_X]/1 mL; GOLDENSEAL 6 [hp_X]/1 mL; CALCIUM SULFIDE 12 [hp_X]/1 mL; SODIUM CHLORIDE 6 [hp_X]/1 mL; PHOSPHORUS 12 [hp_X]/1 mL; ANEMONE PULSATILLA 6 [hp_X]/1 mL; SULFUR 12 [hp_X]/1 mL; ANEMONE PULSATILLA 6 [hp_X]/1 mL; SULFUR 12 [hp_X]/1 mL; CALCIUM SULFIDE 12 [hp_X]/1 mL; GOLDENSEAL 6 [hp_X]/1 mL; SODIUM CHLORIDE 6 [hp_X]/1 mL; MATRICARIA CHAMOMILLA 6 [hp_X]/1 mL; ARABICA COFFEE BEAN 6 [hp_X]/1 mL; ONION 6 [hp_X]/1 mL; PHOSPHORUS 12 [hp_X]/1 mL
INACTIVE INGREDIENTS: CITRIC ACID MONOHYDRATE; GLYCERIN; water; GLYCYRRHIZA GLABRA; SODIUM BENZOATE; CITRIC ACID MONOHYDRATE; GLYCERIN; WATER; GLYCYRRHIZA GLABRA; SODIUM BENZOATE

2 to 12 YEARS
CHILDREN'S COLD & COUGH DAY & NIGHT TIME

DAYTIME

Drug Facts

Active ingredients | Purpose
Allium Cepa 6X HPUS | watery/runny nose, cold, hacking cough, painful throat
Hepar Sulph Calc 12X HPUS | cold, sneezing
Hydrastis 6X HPUS | rattling/tickling cough, sinus congestion, dry, raw, sore throat
Natrum Muriaticum 6X HPUS | dry cough, sore throat
Phosphorus 12X HPUS | hoarse/dry cough, nasal congestion, chest congestion
Pulsatilla 6X HPUS | moist cough, cold, nasal congestion
Sulphur 12X HPUS | chest congestion, nasal congestion, sneezing, runny nose

"HPUS" indicates that the active ingredients are in the official Homeopathic Pharmacopoeia of the United States.

Uses

- temporarily relieves the symptoms of common cold including nasal and chest congestion, runny nose, sore throat, sneezing and cough.

Warnings

PREGNANCY OR BREAST FEEDING

As with any drug, ask a doctor before use if pregnant or breast-feeding.

KEEP OUT OF REACH OF CHILDREN

Keep this and all medications out of the reach of children. In case of accidental overdose, contact a medical professional or a poison control center immediately.

ASK DOCTOR

Consult a physician if:

- symptoms persistent for more than 7 days or worsen
- inflammation, fever or infection develops
- symptoms are accompanied by high fever (over 101° F)
- cough tends to recur or is accompanied by high fever, rash or persistent headache

Do not use this product for persistent or chronic cough such as asthma, smoking or emphysema or if cough is accompanied by excessive phlegm (mucus), unless directed by a licensed medical professional.

WARNINGS

A persistent cough may be a sign of a serious condition.

Sore throat warning: Severe or persistent sore throat or sore throat accompanied by high fever, headache, nausea and vomiting may be serious. Consult a doctor promptly.

In case of emergency, contact a medical professional or Poison Control Center immediately.

Directions

- Measure only with the dosing cup provided.
- Do not use dosing cup with other products.
- On dosing cup, mL= milliliter, tsp = teaspoon.

Children 2 years to under 6 years | 1 teaspoon or 5 mL up to 6 times per day (every 4 hours)
Children 6 years to under 12 years | 2 teaspoons or 10 mL up to 6 times per day (every 4 hours)
Adults and children 12 years and over | 3 teaspoons or 15 mL up to 6 times per day (every 4 hours)

Inactive ingredients

Citric Acid, Glycerin, Glycyrrhiza Extract, Purified Water, Sodium Benzoate.

NIGHTTIME

Drug Facts

Active ingredients | Purpose
Allium Cepa 6X HPUS | watery/runny nose, cold, hacking cough, painful throat
Chamomilla 6X HPUS | sensitive, irritable, fussy, nocturnal occasional sleeplessness
Coffea Cruda 6X HPUS | occasional sleeplessness, restlessness
Hepar Sulph Calc 12X HPUS | cold, sneezing
Hydrastis 6X HPUS | rattling/tickling cough, sinus congestion, dry/raw/sore throat
Natrum Muriaticum 6X HPUS | dry cough, sore throat
Phosphorus 12X HPUS | hoarse/dry cough, nasal congestion, chest congestion
Pulsatilla 6X HPUS | moist cough, cold, nasal congestion
Sulphur 12X HPUS | chest congestion, nasal congestion, sneezing, runny nose

HPUS" indicates that the active ingredients are in the official Homeopathic Pharmacopoeia of the United States.

Uses

- temporarily relieves the symptoms of the common cold including cough, runny nose, sneezing, nasal and chest congestion, and sore throat with accompanying occasional sleeplessness.

Warnings

PREGNANCY OR BREAST FEEDING

As with any drug, ask a doctor before use if pregnant or breast-feeding.

ASK DOCTOR

Consult a physician if:

- symptoms persistent for more than 7 days or worsen
- inflammation, fever or infection develops
- symptoms are accompanied by high fever (over 101° F)
- cough tends to recur or is accompanied by high fever, rash or persistent headache

KEEP OUT OF REACH OF CHILDREN

Keep this and all medications out of the reach of children. In case of accidental overdose, contact a medical professional or a poison control center immediately.

Do not use this product for persistent or chronic cough such as asthma, smoking or emphysema or if cough is accompanied by excessive mucus, unless directed by a licensed health care professional.

WARNINGS

A persistent cough may be a sign of a serious condition.

Sore throat warning: Severe or persistent sore throat or sore throat accompanied by high fever, headache, nausea and vomiting may be serious. Consult a doctor promptly.

In case of emergency, contact a medical professional or Poison Control Center immediately.

Directions

- Measure only with the dosing cup provided.
- Do not use dosing cup with other products.
- On dosing cup, mL= milliliter, tsp = teaspoon.

Children 2 years to under 6 years | 1 teaspoon or 5 mL up to 6 times per day (every 4 hours)
Children 6 years to under 12 years | 2 teaspoons or 10 mL up to 6 times per day (every 4 hours)
Adults and children 12 years and over | 3 teaspoons or 15 mL up to 6 times per day (every 4 hours)

Inactive ingredients

Citric Acid, Glycerin, Glycyrrhiza Extract, Purified Water, Sodium Benzoate.

Questions or comments?
Call 1-866-254-3900.

THIS INFORMATION IS BASED UPON TRADITIONAL HOMEOPATHIC PRACTICE. THESE HAVE NOT BEEN REVIEWED BY FOOD AND DRUG ADMINISTRATION

OTHER SAFETY INFORMATION

TAMPER-EVIDENT: DO NOT USE IF IMPRINTED SHRINK BAND OR SEAL UNDER CAP IS BROKEN OR MISSING

Distributed by:

RITE AID, 30 HUNTER LANE,
CAMP HILL, PA 17011
www.riteaid.com

PACKAGE LABEL - KIT CARTON

CHILDREN'S COLD & COUGH

Sugar Free, Dye Free

Alcohol free

DAYTIME

Cough
Nasal Congestion
Runny Nose
Sore Throat
Sneezing

NIGHTTIME

Cough
Sneezing
Runny Nose
Sleeplessness
Sore Throat

2-12 YEARS

TWO - 4 FL. OZ. (118 mL) Bottles (1 Day, 1 Night)

HOMEOPATHIC